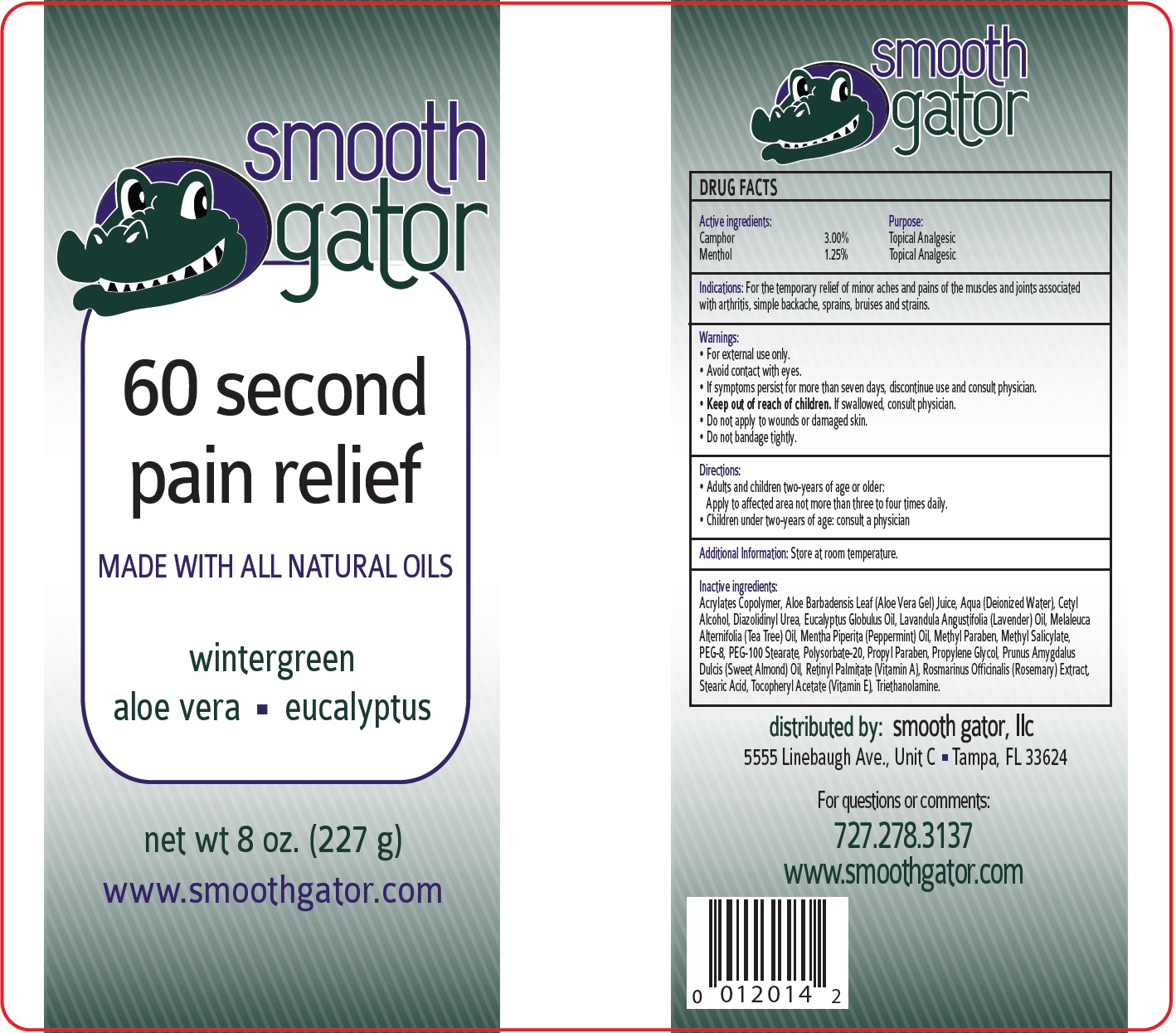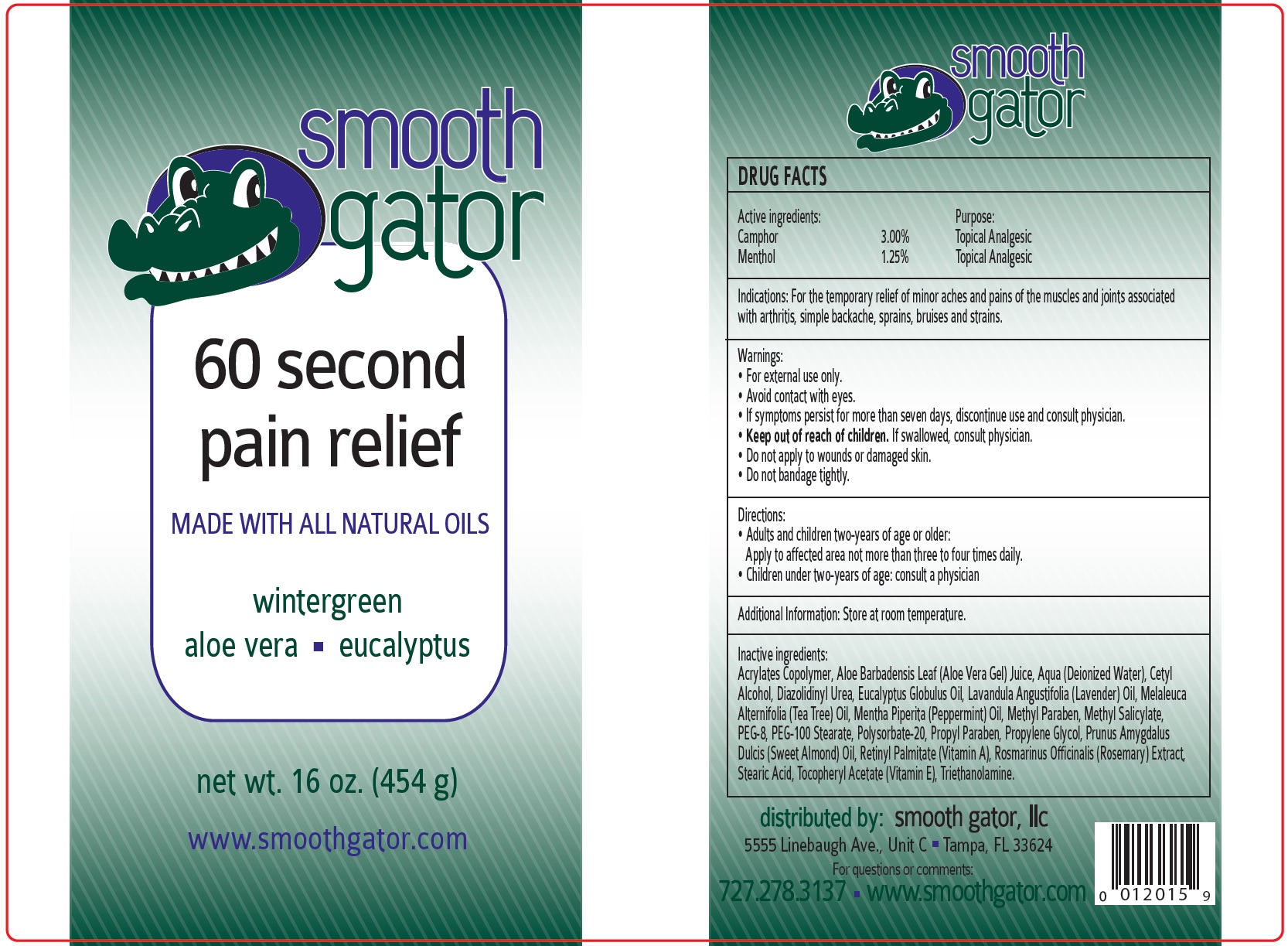 DRUG LABEL: SMOOTH GATOR 60-second Pain Relief
NDC: 70673-298 | Form: CREAM
Manufacturer: Smooth Gator LLC
Category: otc | Type: HUMAN OTC DRUG LABEL
Date: 20231110

ACTIVE INGREDIENTS: CAMPHOR (SYNTHETIC) 30 mg/1 g; MENTHOL 12.5 mg/1 g
INACTIVE INGREDIENTS: ALOE VERA LEAF; WATER; CETYL ALCOHOL; DIAZOLIDINYL UREA; EUCALYPTUS OIL; LAVENDER OIL; TEA TREE OIL; PEPPERMINT OIL; METHYLPARABEN; METHYL SALICYLATE; POLYETHYLENE GLYCOL 400; PEG-100 STEARATE; POLYSORBATE 20; PROPYLPARABEN; PROPYLENE GLYCOL; ALMOND OIL; VITAMIN A PALMITATE; ROSEMARY; STEARIC ACID; .ALPHA.-TOCOPHEROL ACETATE; TROLAMINE

SMOOTH GATOR 60-second Pain Relief

Active ingredients:

Camphor 3.00%

Menthol 1.25%

Purpose:

Topical Analgesic

Indications:

For the temporary relief of minor aches and pains of the muscles and joints associated with arthritis, simple backache, sprains, bruises and strains.

Warnings:

- For external use only.
- Avoid contact with eyes.
- If symptoms persist for more than seven days, discontinue use and consult physician.

Keep out of reach of children.

- If swallowed, consult physician.
- Do not apply to wounds or damaged skin.
- Do not bandage tightly.

Directions:

- Adults and children two-years of age or older:

- Children under two-year of age: consult a physician

Apply to affected area not more than three to four times daily.

Additional Information:

Store at room temperature.

Inactive ingredients:

Acrylates Copolymer, Aloe Barbadensis Leaf (Aloe Vera Gel) Juice, Aqua (Deionized Water), Cetyl Alcohol, Diazolidinyl Urea, Eucalyptus Globulus Oil, Lavandula Angustifolia (Lavender) Oil, Melaleuca Alternifolia (Tea Tree) Oil, Mentha Piperita (Peppermint) Oil, Methyl Paraben, Methyl Salicylate, PEG-8, PEG-100 Stearate, Polysorbate-20, Propyl Paraben, Propylene Glycol, Prunus Amygdalus Dulcis (Sweet Almond) Oil, Retinyl Palmitate (Vitamin A), Rosmarinus Officinalis (Rosemary) Extract, Stearic Acid, Tocopheryl Acetate (Vitamin E), Triethanolamine.